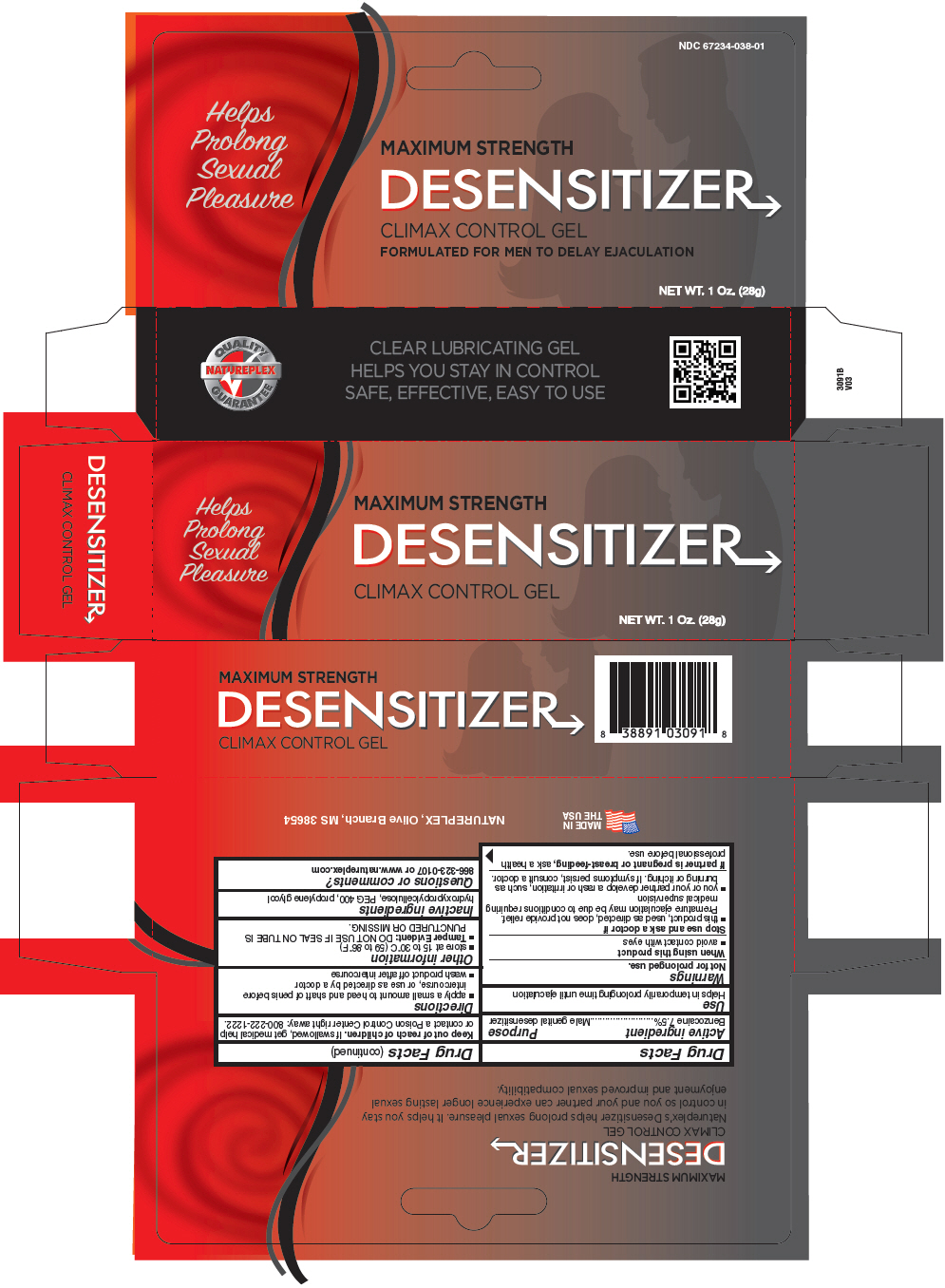 DRUG LABEL: Climax Control 
NDC: 67234-038 | Form: GEL
Manufacturer: Natureplex LLC
Category: otc | Type: HUMAN OTC DRUG LABEL
Date: 20210701

ACTIVE INGREDIENTS: Benzocaine 0.075 g/1 g
INACTIVE INGREDIENTS: HYDROXYPROPYL CELLULOSE, UNSPECIFIED; POLYETHYLENE GLYCOL 400; PROPYLENE GLYCOL

Climax Control Gel
Benzocaine 7.5%

Drug Facts

Active ingredient

Benzocaine 7.5%

Purpose

Male genital desensitizer

Use

Helps in temporarily prolonging time until ejaculation

Warnings

Not for prolonged use.

When using this product

- avoid contact with eyes

Stop use and ask a doctor if

- this product, used as directed, does not provide relief. Premature ejaculation may be due to conditions requiring medical supervision
- you or your partner develop a rash or irritation, such as burning or itching. If symptoms persist, consult a doctor.

PREGNANCY OR BREAST FEEDING

If partner is pregnant or breast-feeding, ask a health professional before use.

Keep out of reach of children. If swallowed, get medical help or contact a Poison Control Center right away: 800-222-1222.

Directions

- apply a small amount to head and shaft of penis before intercourse, or use as directed by a doctor
- wash product off after intercourse

Other information

- store at 15 to 30°C (59 to 86°F)
- Tamper Evident: DO NOT USE IF SEAL ON TUBE IS PUNCTURED OR MISSING.

Inactive ingredients

hydroxypropylcellulose, PEG 400, propylene glycol

Questions or comments?

866-323-0107 or www.natureplex.com

PRINCIPAL DISPLAY PANEL - 28 g Tube Carton

Helps
Prolong
Sexual
Pleasure

MAXIMUM STRENGTH
DESENSITIZER

CLIMAX CONTROL GEL

NET WT. 1 Oz. (28g)